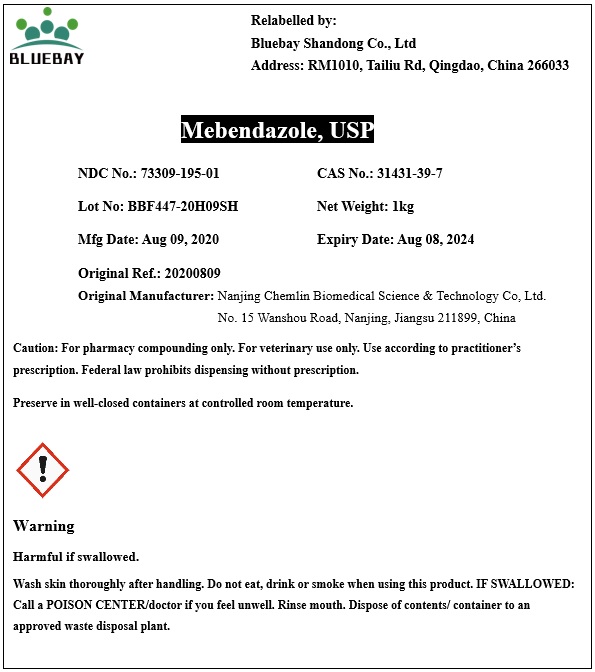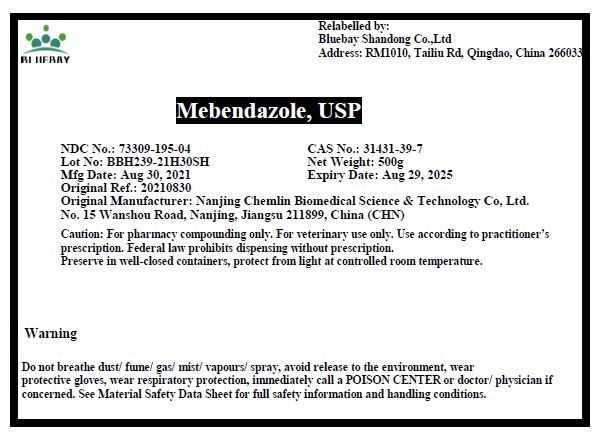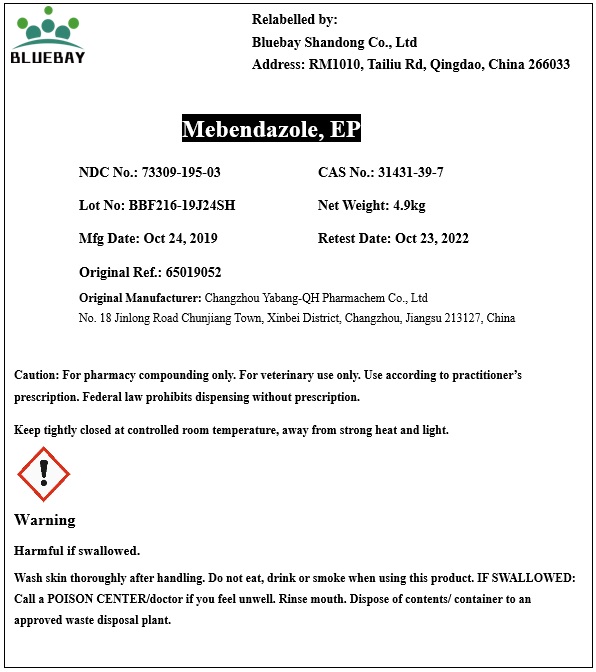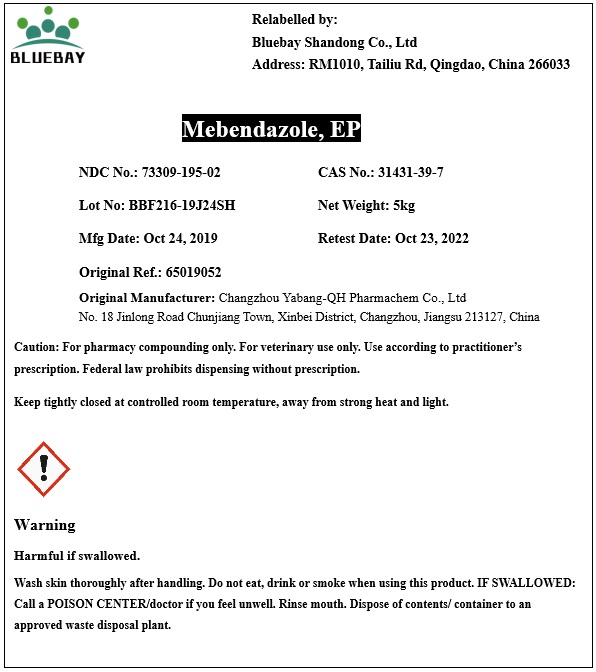 DRUG LABEL: Mebendazole
NDC: 73309-195 | Form: POWDER
Manufacturer: BLUEBAY SHANDONG CO.,LTD
Category: other | Type: BULK INGREDIENT - ANIMAL DRUG
Date: 20220617

ACTIVE INGREDIENTS: MEBENDAZOLE 1 kg/1 kg

Mebendazole